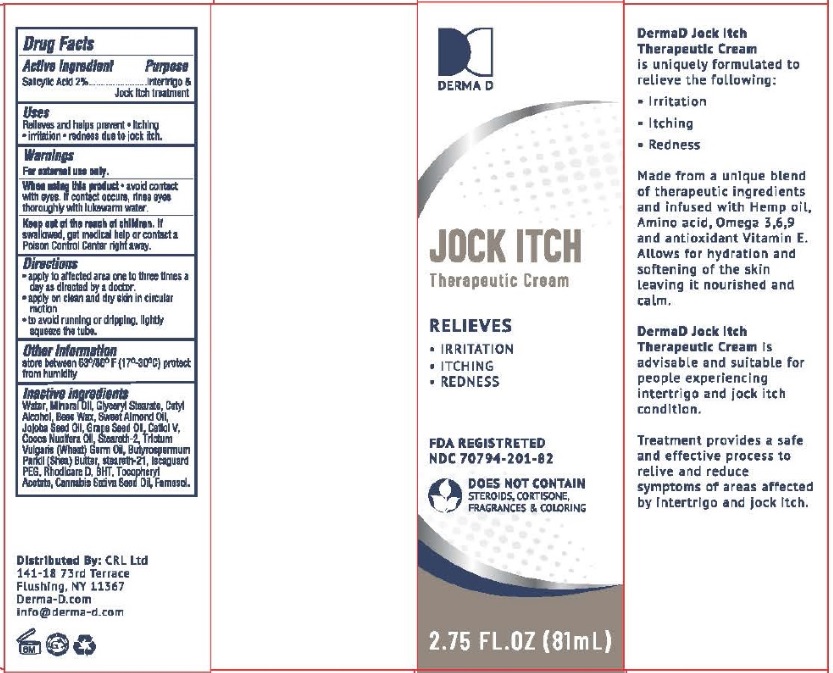 DRUG LABEL: DermaD JOCK ITCH Therapeutic
NDC: 70794-201 | Form: CREAM
Manufacturer: Chen Cohen Industries Inc.
Category: otc | Type: HUMAN OTC DRUG LABEL
Date: 20250529

ACTIVE INGREDIENTS: SALICYLIC ACID 20 mg/1 g
INACTIVE INGREDIENTS: WATER; MINERAL OIL; GLYCERYL MONOSTEARATE; CETYL ALCOHOL; YELLOW WAX; ALMOND OIL; JOJOBA OIL; GRAPE SEED OIL; DECYL OLEATE; COCONUT OIL; WHEAT GERM OIL; STEARETH-2; STEARETH-21; SHEA BUTTER; .ALPHA.-TOCOPHEROL; BUTYLATED HYDROXYTOLUENE; FARNESOL; CANNABIS SATIVA SEED OIL

Drug Facts

Active Ingredient

Salicylic Acid....2%

Purpose

Intertrigo & Jock Itch treatment

Uses

Relieves and helps prevent

- itching
- irritation
- redness due to jock itch

Warnings

For external use only

When using this product

avoid contact with eyes. If contact occurs, rinse eyes thoroughly with lukewarm water.

Keep out of reach of children

If swallowed, get medical help or contact a Poison Control Center right away.

Directions

- Apply to the affected area one to three times a day or as directed by a doctor.
- Apply on clean and dry skin in circular motion.
- To avoid running or dripping, lightly squeeze the tube.

Other Information

Store between 63°/80°F (17-30C)

Protect from humidity.

Inactive Ingredients

Water, Mineral Oil, Glyceryl Stearate, Cetyl Alcohol, Bees Wax, Sweet Almond Oil, Jojoba Seed Oil. Grape Seed Oil, Cetlol V, Cocos Nucifera Oil, Steareth-2, Trictum Vulgaris (Wheat) Germ Oil, Butyrospermum Parkii (Shea Butter), Steareth-21, Iscaguard PEG, Rhodicare D, BHT, Tocopheryl Acetate, Cannabis Sativa Seed Oil, Farnesol.

Principal Display Panel

NDC 70794-201-82

DERMAD JOCK ITCH Therapeutic Cream

RELIEVES

- IRRITATION
- ITCHING
- REDNESS

FDA REGISTERED

DOES NOT CONTAIN STEROIDS, CORTISONE, FRAGRANCES AND COLORING

2.75 FL. OZ (81 mL)